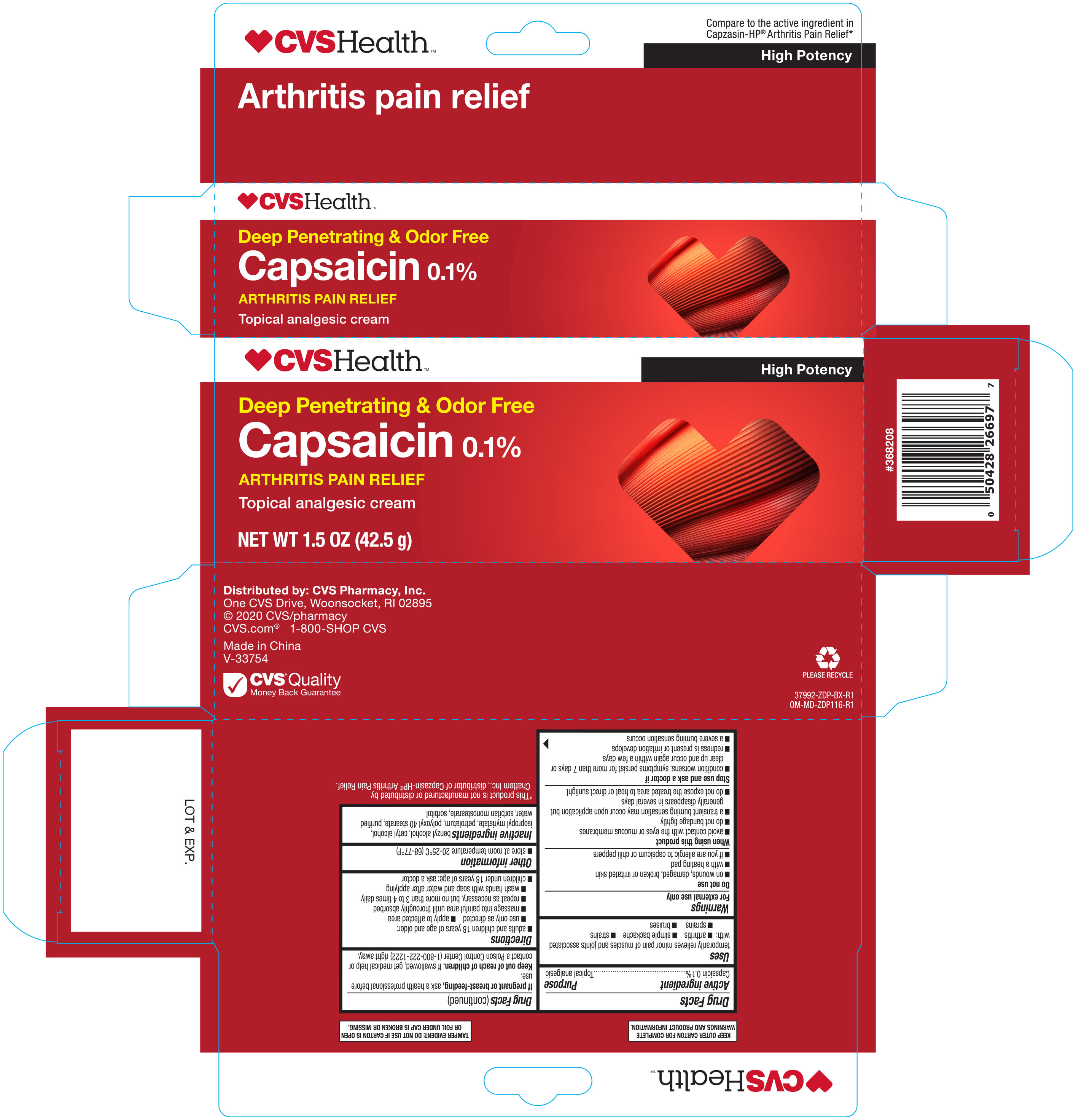 DRUG LABEL: CVS CAPSAICIN
NDC: 59779-381 | Form: CREAM
Manufacturer: CVS PHARMACY
Category: otc | Type: HUMAN OTC DRUG LABEL
Date: 20251030

ACTIVE INGREDIENTS: CAPSAICIN 0.1 g/100 g
INACTIVE INGREDIENTS: CETYL ALCOHOL; POLYOXYL 40 STEARATE; BENZYL ALCOHOL; SORBITAN MONOSTEARATE; ISOPROPYL MYRISTATE; SORBITOL; PETROLATUM; WATER

CVS Capsaicin Cream 0.1% 1.5 oz 37992 ZDP

Active ingredient Purpose

Capsaicin 0.1%........................................................................Topical analgesic

PURPOSE

For the temporary relief of minor pain associated with:

- Arthritis
- Simple backache
- Muscle strains
- Sprains
- Bruises

Warnings

For external use only

Do not use

- on wounds, damaged, broken or irritated skin
- with a heating pad
- if you are allergic to capsicum or chili peppers

When using this product

- avoid contact with eyes and mucous membranes
- do not bandage tightly
- a transient burning sensation may occur upon applications but generally disappears in several days
- do not expose the treated area to heat or direct sunlight

Stop use and ask a doctor if

- condition worsens
- symptoms persist for more than 7 days or clear up and occur again within a few days
- redness is present or irritation develops
- a severe burning sensation occurs

PREGNANCY OR BREAST FEEDING

If pregnant or breast-feeding, ask a health professional before use.

Keep out of reach of children.

In case of accidental ingestion, get medical help or contact a Poison Control Center right away.

Directions

Adults and children over 18 years:

- use only as directed
- apply to affected area
- massage into painful area until thoroughly absorbed
- repeat as necessary, but no more than 3 to 4 times daily
- wash hands with soap and water after applying
- children under 18 years of age: ask a doctor

Inactive ingredients

benzyl alcohol, cetyl alcohol, isopropyl myristate, petrolatum, polyoxyl 40 stearate, water, sorbitan monostearate, sorbitol

DOSAGE AND ADMINISTRATION

Distributed by: CVS Pharmacy, Inc.

One CVS Drive, Woonsocket, RI 02895

www.cvs.com

Made in China

Other information

- store at room temperature
- Lot No. and Exp. Date: see box or crimp of tube
- save carton for complete Drug Facts information